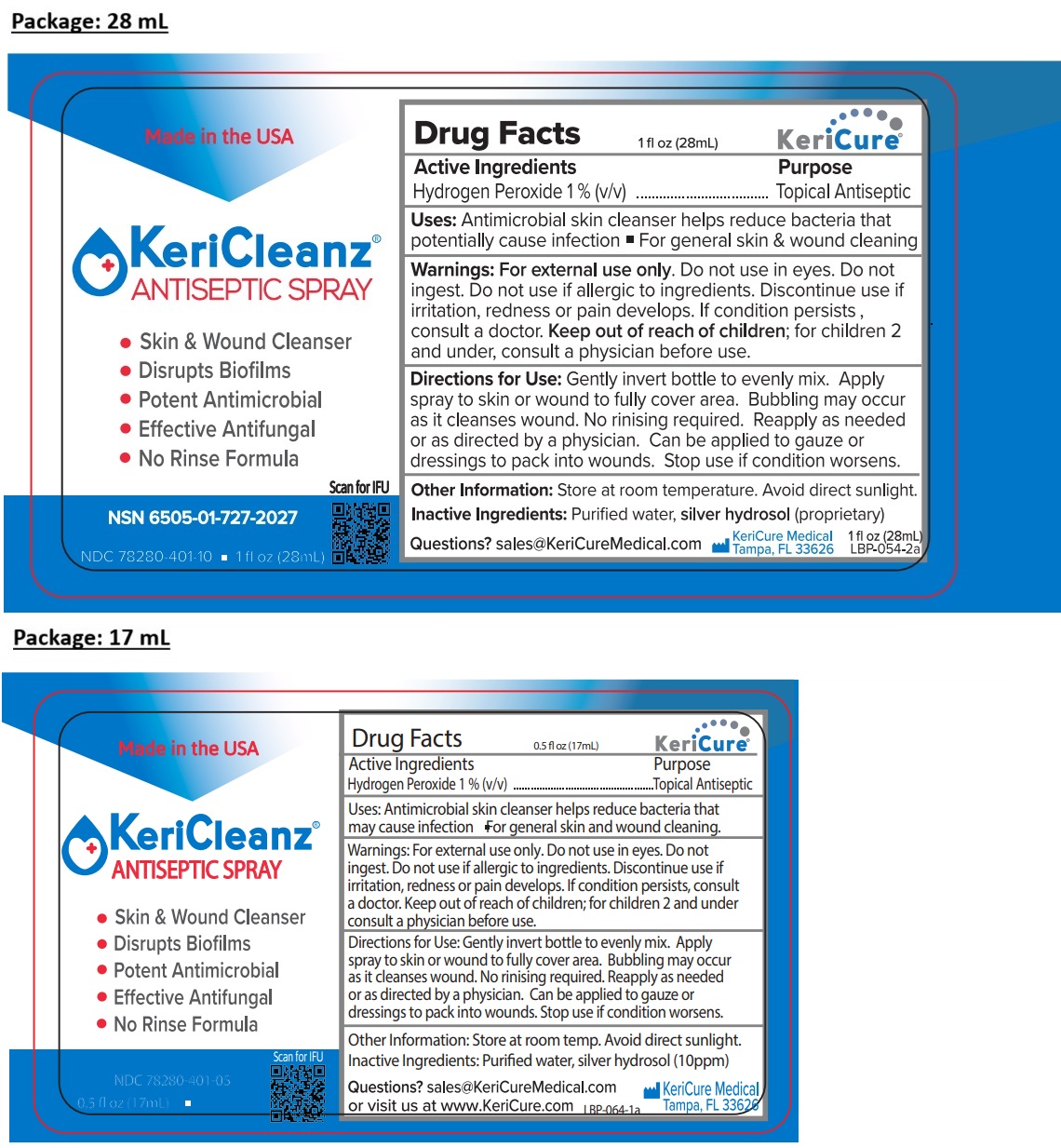 DRUG LABEL: KeriCleanz ANTISEPTIC
NDC: 78280-401 | Form: SPRAY
Manufacturer: Kericure Inc.
Category: otc | Type: HUMAN OTC DRUG LABEL
Date: 20250731

ACTIVE INGREDIENTS: HYDROGEN PEROXIDE 1 mL/100 mL
INACTIVE INGREDIENTS: WATER; SILVER

KeriCleanz® ANTISEPTIC SPRAY

Active Ingredients

Hydrogen Peroxide 1% (v/v)

Purpose

Topical Antiseptic

Uses:

Antimicrobial skin cleanser helps reduce bacteria that potentially cause infection • For general skin & wound cleaning.

Warnings:

For external use only. Do not use in eyes. Do not ingest. Do not use if allergic to ingredients. Discontinue use if irritation, redness or pain develops. If condition persists, consult a doctor.

Keep out of reach of children; for children 2 and under consult a physician before use.

Directions for Use:

Gently invert bottle to evenly mix. Apply spray to skin or wound to fully cover area. Bubbling may occur as it cleanses wound. No rinsing required. Reapply as needed or as directed by a physician. Can be applied to gauze or dressings to pack into wounds. Stop use if condition worsens.

Other Information:

Store at room temperature. Avoid direct sunlight.

Inactive Ingredients:

Purified water, silver hydrosol (10ppm)

Questions?

sales@KeriCureMedical.com or visit us at www.KeriCure.com

Made in the USA

• Skin and Wound Cleanser
• Disrupts Biofilms
• Potent Antimicrobial
• Effective Antifungal
• No Rinse Formula

KeriCure Medical Tampa, FL 33626